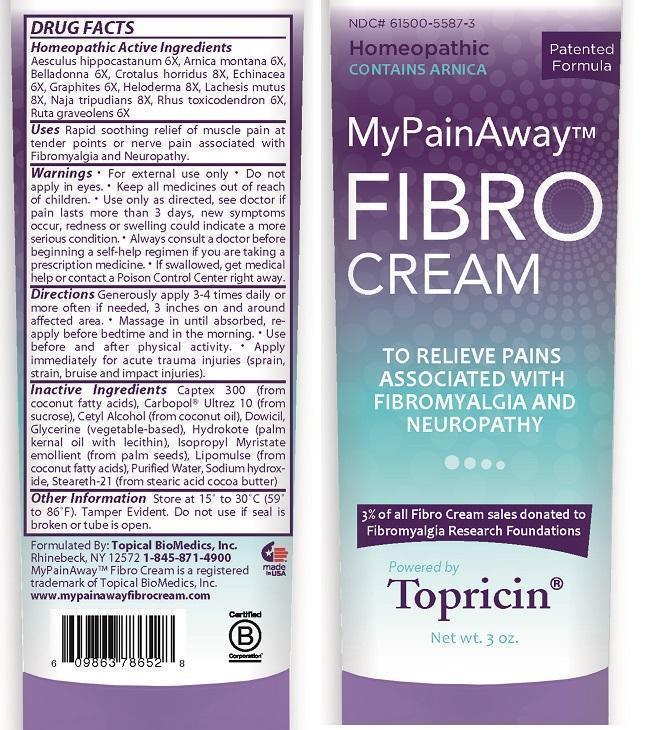 DRUG LABEL: My Pain Away
NDC: 61500-5587 | Form: CREAM
Manufacturer: Topical BioMedics, Inc.
Category: homeopathic | Type: HUMAN OTC DRUG LABEL
Date: 20140620

ACTIVE INGREDIENTS: AESCULUS HIPPOCASTANUM FLOWER 6 [hp_X]/88 mL; ARNICA MONTANA 6 [hp_X]/88 mL; ATROPA BELLADONNA 6 [hp_X]/88 mL; CROTALUS HORRIDUS HORRIDUS VENOM 8 [hp_X]/88 mL; ECHINACEA ANGUSTIFOLIA  6 [hp_X]/88 mL; GRAPHITE 6 [hp_X]/88 mL; HELODERMA HORRIDUM VENOM 8 [hp_X]/88 mL; LACHESIS MUTA VENOM 8 [hp_X]/88 mL; NAJA NAJA VENOM 8 [hp_X]/88 mL; TOXICODENDRON PUBESCENS LEAF 6 [hp_X]/88 mL; RUTA GRAVEOLENS FLOWERING TOP 6 [hp_X]/88 mL
INACTIVE INGREDIENTS: COCONUT ACID; SUCROSE; CETYL ALCOHOL; QUATERNIUM-15 CIS-FORM; GLYCERIN; PALM KERNEL OIL; ISOPROPYL MYRISTATE; WATER; SODIUM HYDROXIDE; STEARETH-12

My Pain Away Fibro Cream
Drug Facts

Homeopathic Active Ingredients:

Aesculus hippocastanum 6X, Arnica montana 6X, Belladonna 6X, Crotalus horridus 8X, Echinacea 6X, Graphites 6X, Heloderma 8X, Lachesis mutus 8X, Naja tripudians 8X, Rhus toxicodendron 6X, Ruta graveolens 6X

Uses:

Rapid soothing relief of muscle pain at tender points or nerve pain associated with Fibromyalgia and Neuropathy.

Warnings

For external use only

Do not apply in eyes.

Keep all medicines out of reach of children.

STOP USE

Use only as directed, see doctor if pain last more than 3 days, new symptoms occur, redness or swelling could indicate a more serious condition.

ASK DOCTOR

Always consult a doctor before beginning a self-help regimen if you are taking a prescription medicine.

If swallowed, get medical help or contact a Poison Control Center right away.

Directions:

Generously apply 3-4 times daily or more often if needed, 3 inches on and around affected area. Massage in until absorbed, reapply before bedtime and in the morning. Use before and after physical activity. Apply immediately for acute trauma injuries (sprain, strain, bruise and impact injuries).

Inactive Ingredients:

Captex 300 (from coconut fatty acids), Carbopol® Ultrez 10 (from sucrose), Cetyl Alcohol (from coconut oil), Dowicil, Glycerine (Vegetable-based), Hydrokote (palm kernal oil with lecithin), Isopropyl Myristate emollient (from palm seeds), Lipomulse (from coconut fatty acids), Purified Water, Sodium hydroxide, Steareth-12 (from stearic acid cocoa butter)

Other Information:

Store at 15° to 30°C (59° to 86°F). Tamper Evident: Do not use if tube is punctured, cut or opened.

QUESTIONS

Formulated by: Topical BioMedics, Inc.

Rhinebeck, NY 12572 1-845-871-4900

MyPainAway™ Fibro Cream is a registered trademark of Topical BioMedics, Inc.

www.mypoinawayfibrocream.com

Principal Display Panel 3 oz

Homeopathic

Contains Arnica

MyPainAway™

Fibro Cream

To Relieve Pains Assoicated with Fibromyalgia and Neuropathy

3% of all Fibro Cream sales donated to Fibromyalgia Research Foundations

Powerd by Topricin®